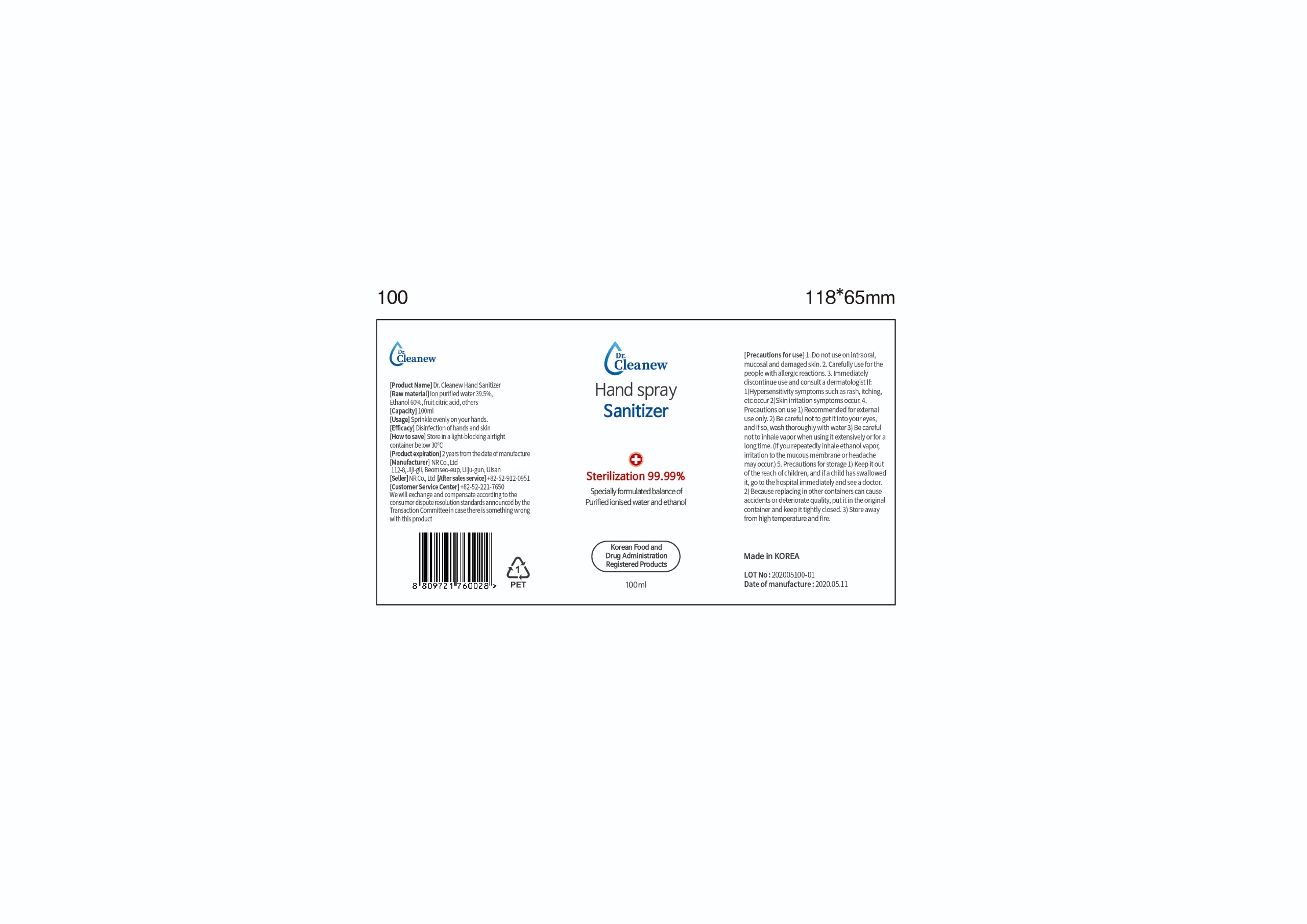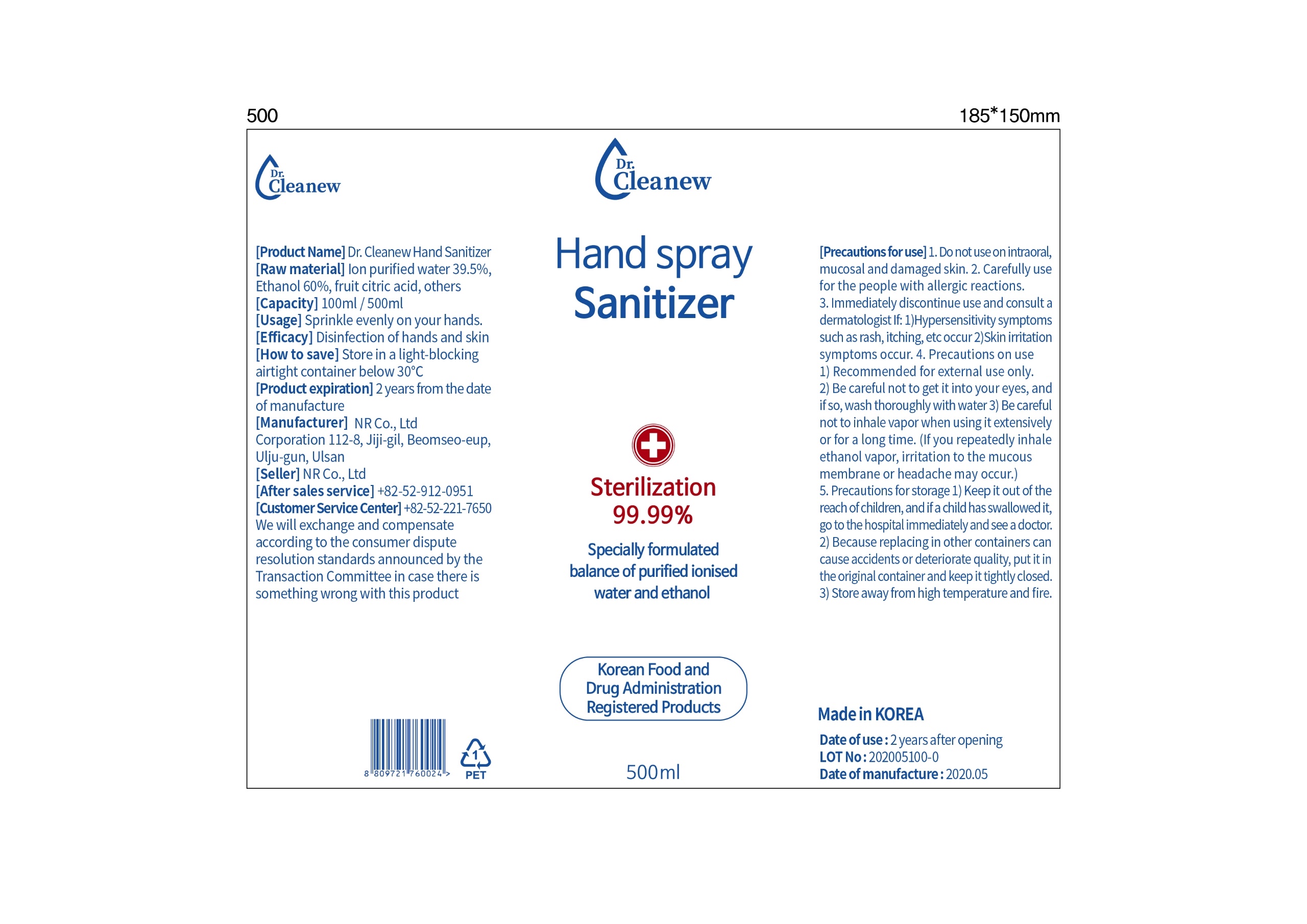 DRUG LABEL: Dr.Cleanew Hand Sanitizer
NDC: 79191-301 | Form: LIQUID
Manufacturer: NR CO.,Ltd.
Category: otc | Type: HUMAN OTC DRUG LABEL
Date: 20200624

ACTIVE INGREDIENTS: ALCOHOL 60 mL/100 mL
INACTIVE INGREDIENTS: CITRIC ACID MONOHYDRATE 0.5 mL/100 mL; WATER 39.5 mL/100 mL

SANITIZER

PURPOSE

Antimicrobial

Active Ingredients

ALCOHOL

Use

Hand sanitizer to help reduce bacteria that potentially can cause disease.
Recommended for external use only.

Warnings

For external use only

Keep away from fire of flame

Do not spray on clothes because it can stain.

Be caeful not to get into your eyes, and if so wash thoroughly with water

Keep out of reach of children

Stop use and ask a doctor

Take care not to get into the eye.

If a children has swallowed it go to the hospital immediately and see a doctor

Other information

beause replacing in other containers can cause accidents or deteriorate quality, put it in the original container and keep

it tightly closed.

store away from high temperature and fire.

indication

sprinkle evenly on your hands

do not use on intraoral, mucosal and damaged skin

carefully use for the people with allergic reactions,

immediately discontinue use and consult a dermatologist if hypersensitivity symptoms

such as rash itching etc occur

skin irritation symptoms occur

inactive ingredient

water, citric acid

Direction

disinfection of hands and skin

Spray on hands or spray where disinfection is needed

label

79191-301-01

79191-301-02